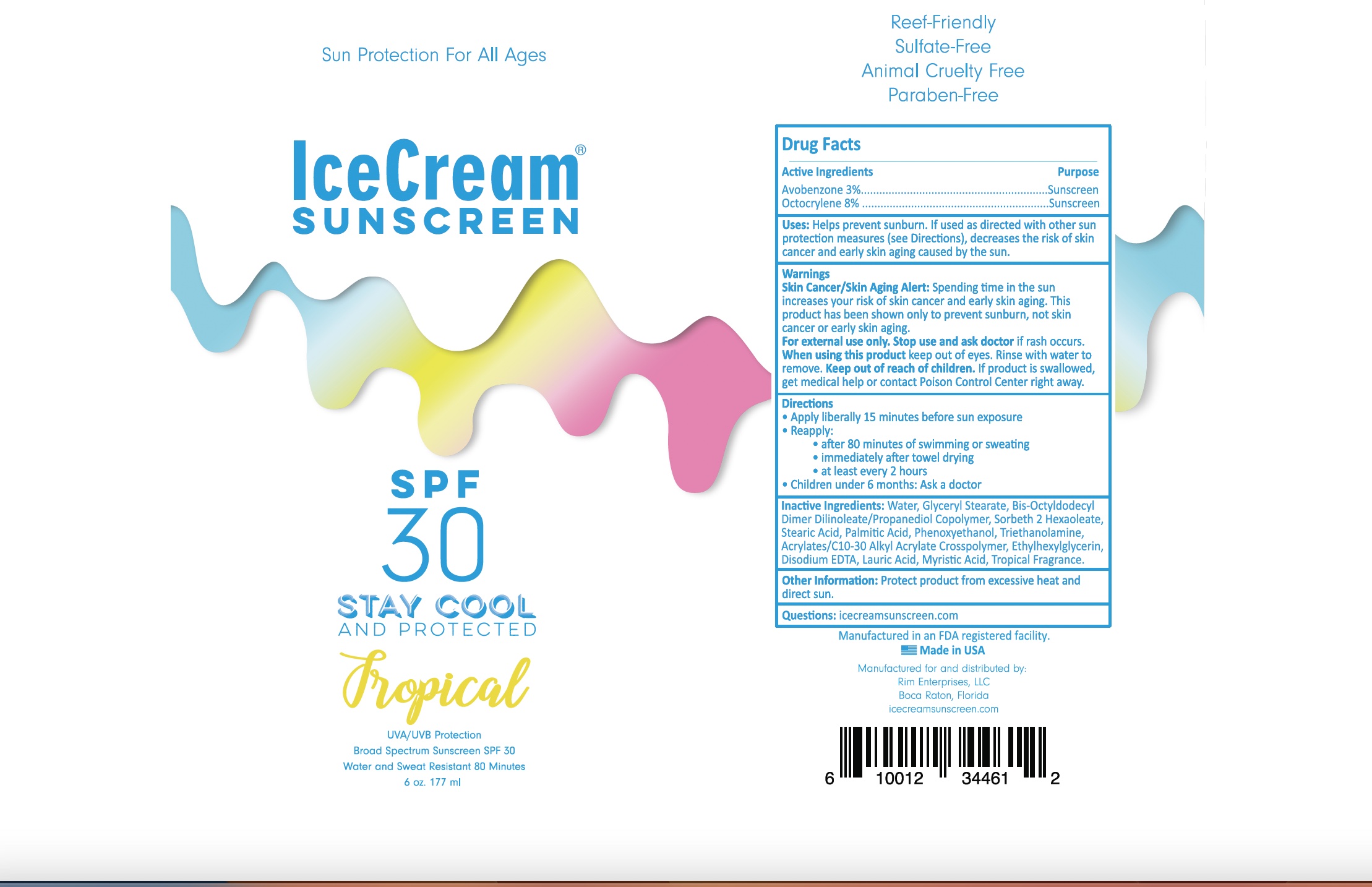 DRUG LABEL: 2000DL-CL30T
NDC: 58418-004 | Form: LOTION
Manufacturer: Epic Laboratories, LLC
Category: otc | Type: HUMAN OTC DRUG LABEL
Date: 20241231

ACTIVE INGREDIENTS: Octocrylene 2.34 g/30 mL; AVOBENZONE 0.9 g/30 mL
INACTIVE INGREDIENTS: ETHYLHEXYLGLYCERIN; WATER; EDETATE DISODIUM ANHYDROUS; SORBETH-12 HEXAOLEATE; BIS-OCTYLDODECYL DIMER DILINOLEATE/PROPANEDIOL COPOLYMER; PHENOXYETHANOL; CARBOMER COPOLYMER TYPE A (ALLYL PENTAERYTHRITOL CROSSLINKED); STEARIC ACID; TROLAMINE; GLYCERYL MONOSTEARATE; FRAGRANCE 13576

Tropical scented SPF30 BROAD SPECTRUM LOTION
FORMULA #2000-DL-CL30V
Oxybenzone free/Octinoxate free

Active Ingredients:

Avobenzone 3%

Octocrylene 8%

Purpose:

Sunscreen

INDICATIONS AND USAGE

Uses: Helps prevent sunburn. If used as directed with other sun protection measures (see Directions), decreases the risk

of skin cancer and early skin aging caused by the sun.

WARNINGS

WARNINGS: Skin Cancer/ Sking Aging Alert: Spending time in the sun

increases your risk of skin cancer and early skin aging. This product has been shown only to prevent sunburn, not skin cancer and early skin aging.

For external use only.

When using this product keep out of eyes. Rinse with water to remove.

Stop use and ask a doctor if irritation or rash occurs.

Keep out of reach of children. If product is swallowed, get immediate medical help or contact a Poison Control Center

right away.

Directions:

- apply liberally 15 minutes before sun exposure
- reapply:

*after 80minutes of swimming or sweating * immediately after towel drying

*at least every 2 hours

*children under 6 months: Ask a doctor

DOSAGE AND ADMINISTRATION

Uses: Helps prevent sunburn. If used as directed with other sun protection measures (see Directions), decreases the risk of skin cancer and early skin aging caused by the sun.

INACTIVE INGREDIENT

Inactive Ingredients: Water, Acrylates/C10-30, Alkyl Acrylate cross polymer, Stearic Acid, Glyceryl Monostearate, Bis-Octyldodecyl Dimer Dillinoleate/Propanediol Copolymer, Sorbeth-2-Hexaoleate, Phenoxylethanol, Ethylhexylglycerin, Triethanolamine, Disodium EDTA.

OTHER SAFETY INFORMATION

*Protect product from excessive heat and direct sun

Questions or comments? Call toll free 1-800-535-5053